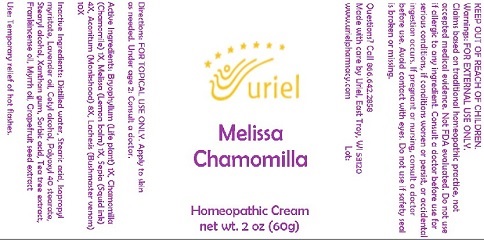 DRUG LABEL: Melissa Chamomilla
NDC: 48951-7196 | Form: CREAM
Manufacturer: Uriel Pharmacy Inc.
Category: homeopathic | Type: HUMAN OTC DRUG LABEL
Date: 20210719

ACTIVE INGREDIENTS: SEPIA OFFICINALIS JUICE 4 [hp_X]/1 g; ACONITUM NAPELLUS 8 [hp_X]/1 g; LACHESIS MUTA VENOM 10 [hp_X]/1 g; KALANCHOE DAIGREMONTIANA LEAF 1 [hp_X]/1 g; MATRICARIA CHAMOMILLA 1 [hp_X]/1 g; MELISSA OFFICINALIS 1 [hp_X]/1 g
INACTIVE INGREDIENTS: LAVENDER OIL; SORBIC ACID; STEARYL ALCOHOL; MYRRH OIL; XANTHAN GUM; TEA TREE OIL; WATER; ISOPROPYL MYRISTATE; CETYL ALCOHOL; POLYOXYL 40 STEARATE; FRANKINCENSE OIL; STEARIC ACID; CITRUS PARADISI SEED

Melissa Chamomilla

INDICATIONS AND USAGE

Directions: FOR TOPICAL USE ONLY.

DOSAGE AND ADMINISTRATION

Apply to skin as needed. Under age 2: Consult a doctor.

ACTIVE INGREDIENT

Active Ingredients: Bryophyllum (Life plant) 1X, Chamomilla (Chamomile) 1X, Melissa (Lemon balm) 1X, Sepia (Squid ink) 4X, Aconitum (Monkshood) 8X, Lachesis (Bushmaster venom) 10X

INACTIVE INGREDIENT

Inactive Ingredients: Distilled water, Stearic acid, Isopropyl myristate, Lavender oil, Cetyl alcohol, Polyoxyl 40 stearate, Stearyl alcohol, Xanthan gum, Sorbic acid, Tea tree extract, Frankincense oil, Myrrh oil, Grapefruit seed extract

PURPOSE

Use: Temporary relief of hot flashes.

KEEP OUT OF REACH OF CHILDREN.

Warnings: FOR EXTERNAL USE ONLY.
Claims based on traditional homeopathic practice, not accepted medical evidence. Not FDA evaluated. Do not use if allergic to any ingredient. Consult a doctor before use for serious conditions, if conditions worsen or persist, or accidental ingestion occurs. If pregnant or nursing, consult a doctor before use. Avoid contact with eyes. Do not use if safety seal is broken or missing.

Questions? Call 866.642.2858
Made with care by Uriel, East Troy, WI 53120
www.urielpharmacy.com Lot: